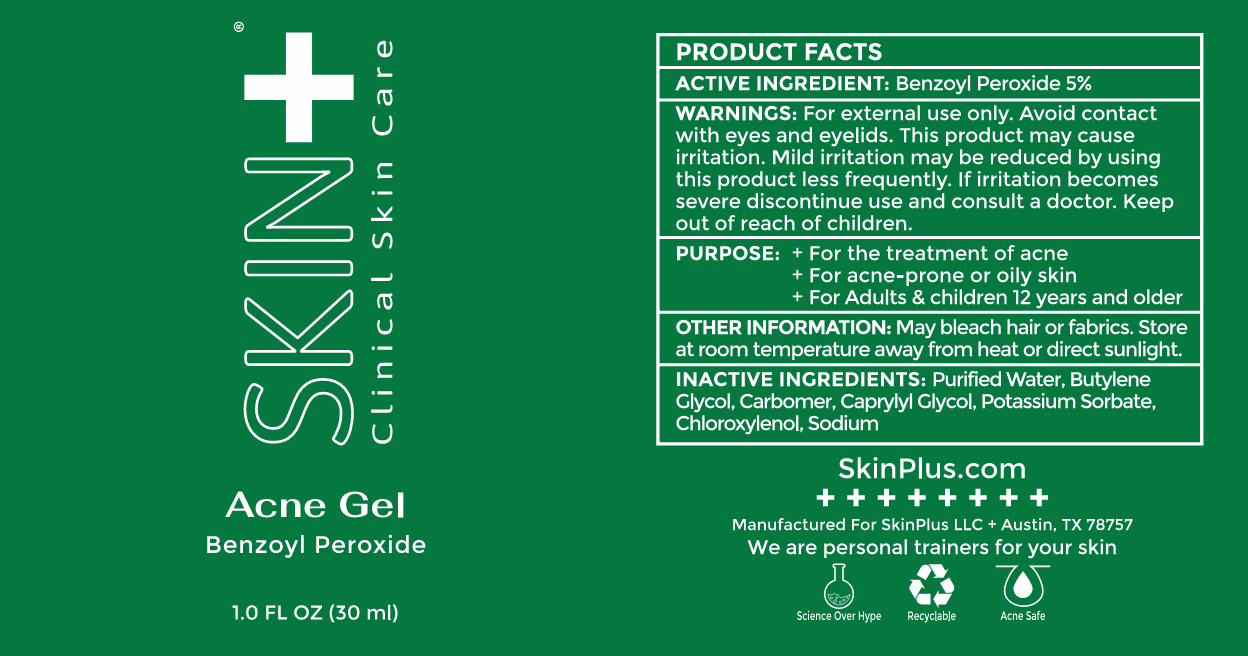 DRUG LABEL: Acne Gel
NDC: 82172-230 | Form: GEL
Manufacturer: SKIN PLUS, LIMITED LIABILITY COMPANY
Category: otc | Type: HUMAN OTC DRUG LABEL
Date: 20230215

ACTIVE INGREDIENTS: BENZOYL PEROXIDE 5 g/100 g
INACTIVE INGREDIENTS: SODIUM HYDROXIDE 0.3 g/100 g; BUTYLENE GLYCOL 12 g/100 g; CARBOMER 940 1 g/100 g

Acne Gel 5%